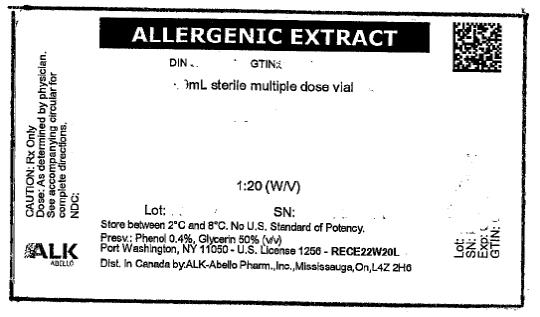 DRUG LABEL: MIXED ASPERGILLUS
NDC: 0268-8036 | Form: INJECTION, SOLUTION
Manufacturer: ALK-Abello, Inc.
Category: other | Type: NON-STANDARDIZED ALLERGENIC LABEL
Date: 20230530

ACTIVE INGREDIENTS: ASPERGILLUS NIGER VAR. NIGER 10000 [PNU]/1 mL; ASPERGILLUS REPENS 10000 [PNU]/1 mL; ASPERGILLUS FLAVUS VAR. ORYZAE 10000 [PNU]/1 mL; ASPERGILLUS TERREUS 10000 [PNU]/1 mL
INACTIVE INGREDIENTS: SODIUM CHLORIDE 0.009 g/1 mL; SODIUM BICARBONATE 0.00275 g/1 mL; PHENOL 0.004 mL/1 mL; GLYCERIN 0.5 mL/1 mL; HYDROCHLORIC ACID; SODIUM HYDROXIDE

THERAPEUTIC ALLERGENIC EXTRACTS- Glycerin Products

DIRECTIONS FOR USE OF

THERAPEUTIC ALLERGENIC EXTRACTS

WARNING

This product is intended for use by physicians who are experienced in the administration of allergenic extracts and the emergency care of anaphylaxis or for use under the guidance of an allergy specialist.

Patients should be instructed to recognize adverse reaction symptoms and cautioned to contact the physician’s office if reaction symptoms occur. As with all allergenic extracts, severe systemic reactions may occur. In certain individuals, these reactions may rarely result in death. Patients should be observed for 20 to 30 minutes following treatment, and emergency measures, as well as personnel trained in their use, should be immediately available in the event of a life-threatening reaction. Patients with unstable asthma or steroid dependent asthmatics and patients with underlying cardiovascular disease are at greater risk. Adverse events are to be reported to Med Watch (1-800-FDA-1088), Adverse Event Reporting , Food and Drug Administration, 5600 Fishers Lane, Rockville, MD 20852-9787.

This product should not be injected intravenously. Deep subcutaneous routes have proven to be safe. Patients receiving beta-blockers may not be responsive to epinephrine or inhaled bronchodilators. Respiratory obstruction not responding to parenteral or inhaled bronchodilators may require theophylline, oxygen, intubation and the use of life support systems. Parenteral fluid and/or plasma expanders may be utilized for the treatment of shock. Adrenocorticosteroids may be administered parenterally or intravenously.

Refer to WARNINGS, PRECAUTIONS, and ADVERSE REACTIONS sections below.

Port Washington, NY 11050

U.S. Government License No. 1256

DESCRIPTION

Sterile therapeutic extracts are supplied in either Phenol Saline Diluent or in Diluent containing Glycerin 50% (v/v) for subcutaneous injection. Inactive ingredients may include: Sodium Chloride for isotonicity, Glycerin, and Sodium Bicarbonate as buffering agents. These products are compounded and diluted on a w/v or PNU basis. Pollens are individually extracted from pure pollen extracted in a phenol-preserved sodium bicarbonate solution. Short Ragweed and Mixed (Tall and Short) Ragweed extracts are standardized by Antigen E content and so labeled. The Antigen E content of extracts containing Short Ragweed at a concentration more dilute than a weight/volume ratio of 1:10 are obtained by calculating the Antigen E content based on the assay value of more concentrated extract. Pollen extracts are filtered aseptically and, after final packaging, they are tested for sterility and safety. Molds are individually extracted from pure powdered inactivated mold source material extracted in phenol preserved saline. Mold extracts are filtered aseptically and after final packaging are tested for sterility and safety. Molds are present in all inhabited places at all seasons of the year; they are so ubiquitous that they are prevalent at times when common allergic pollens and other inhalants are not. In the home and surroundings, molds are found in upholstered furniture, mattresses, drapes, cellar and storage room dust, woolens, leather goods, fruits, meats, cheeses, garden soil and on plants. Spores, mycelial fragments and mold residues are thus inhaled, contacted and ingested continuously.

Miscellaneous inhalants and epidermals are individually extracted in phenol preserved saline, filtered aseptically and after final packaging are tested for sterility and safety.

CLINICAL PHARMACOLOGY

The treatment consists of the subcutaneous injection of gradually increasing doses of the allergens to which the patient is allergic. It has been demonstrated that this method of treatment induces an increased tolerance to the allergens responsible for the symptoms on subsequent exposure. The exact relationships between allergen, skin-sensitizing antibody (IgE) and the blocking antibody (IgG) have not been precisely established. Clinically confirmed immunological studies have adduced evidence of the efficacy of hyposensitization therapy.

Numerous controlled studies have demonstrated the clinical efficacy of immunotherapy with cat, dust mites and some pollen extracts. Nevertheless, responses are variable, and in a few studies patients reported no appreciable benefit.

Extracts containing Short Ragweed pollen bear a labeled potency declaration in terms of Antigen E content. Numerous studies have confirmed Antigen E (AgE) as the major antigen associated with Short Ragweed pollinosis.^1 Therefore, it is essential that the physician be aware of AgE content of allergenic extract administered for hyposensitization therapy.

Some studies have indicated that for most patients a cumulative Antigen E dosage of less than 0.1 unit is not immunizing (sufficient to stimulate specific IgG antibodies).^2 This, however, does not suggest that 0.1 unit is a maximum tolerated dose. Most moderately sensitive patients may tolerate a dosage of ten to fifty times greater. If results with this product are unsatisfactory with exquisitely sensitive patients who cannot tolerate an immunizing dose, the physician should consider alternative therapy.

One well-controlled study demonstrated that standard immunotherapy (gradually increasing doses of antigen given subcutaneously to a maximum tolerated peak dose) using crude ragweed extract of known Antigen E potency, was significantly superior to placebo and low dose immunotherapy (0.1 units AgE cumulative dose) in amelioration of symptoms associated with ragweed hay fever. These patients received a cumulative dose of 18-350 units Antigen E (median = 84.9 units). The maximum single dose ranged from 3.7 to 46.8 units (median = 11.1 units) prior to the ragweed hay fever season.^10

Patients for this study were sensitive to Ragweed Antigen E, as determined by intradermal skin testing at a dose of 0.01 units AgE/mL. A series of 24 weekly injections were administered. Forty-seven percent of the patients experienced at least one systemic reaction with an average of 1.2 systemic reactions per patient. None of the patients were able to achieve the expected maximum dose (90 units of Antigen E) in the 24 weekly injection dosage schedule.

INDICATIONS AND USAGE

Hyposensitization (injection) therapy is a treatment for patients exhibiting allergic reactions to seasonal pollens, dust, molds, animal danders, various other inhalants, and in situations where the offending allergen cannot be avoided.

Prior to initiation of therapy, the clinical sensitivity should be established by careful evaluation of the patient’s history confirmed by diagnostic skin testing. Hyposensitization should not be prescribed for sensitivities to allergens which can easily be avoided.

CONTRAINDICATIONS

A patient should not be immunized with preparations of allergens to which the patient has not demonstrated symptoms, IgE antibodies, positive skin tests, or properly controlled challenge testing. In most cases, immunotherapy is not indicated for those allergens that can be eliminated or minimized by environmental control.

Patients on beta-blockers are not candidates for immunotherapy, as they can be non-responsive to beta-agonists that may be required to reverse a systemic reaction (also see WARNINGS AND ADVERSE REACTIONS).

In the presence of active symptoms such as rhinitis, wheezing, dyspnea, etc., the indication of immunotherapy must be weighed carefully against the risk of temporarily aggravating the symptoms by the injection itself.

Also, there is some evidence, although inconclusive, that routine immunizations may exacerbate autoimmune diseases.^3,4,5 Hyposensitization should be given cautiously to patients with this predisposition. Patients with severe cardiorespiratory symptoms are at an additional risk during a systemic reaction. The physician must weigh risk to benefit in these cases.

WARNINGS

Patients should always be observed for at least 20-30 minutes after any injection. In the event of a marked systemic reaction, application of a tourniquet above the injection site and administration of 0.2 mL to 1 mL (0.01 mg/kg) of Epinephrine Injection (1:1,000) is recommended. Maximal recommended dose for children between 2 and 12 years is 0.5 mL. The tourniquet is then gradually released at 15 minute intervals. Patients under treatment with beta-blockers may be refractory to the usual dose of epinephrine.

Volume expanders and vasopressor agents may be required to reverse hypotension. Inhalation bronchodilators and parenteral aminophylline may be required to reverse bronchospasm. In cases of respiratory obstruction, oxygen and intubation may be necessary. Life-threatening reaction unresponsive to the above may require cardiopulmonary resuscitation.

DO NOT GIVE INTRAVENOUSLY

After inserting the needle, but before injecting the dose, pull plunger of the syringe slightly. If blood returns in the syringe, discard the syringe and contents and repeat injection at another site.

Bulk concentrated extracts must be diluted for initial therapy.

Withhold allergenic extracts temporarily or reduce the dose in patients with any one of the following conditions:

- Severe rhinitis or asthma symptoms;

- Infection or flu accompanied by fever;

- Exposure to excessive amounts of clinically relevant allergen prior to therapy.

Patients with unstable asthma or steroid dependent asthmatics and patients with underlying cardiovascular disease are at greater risk. See PRECAUTIONS AND ADVERSE REACTIONS.

TRANSFER OF PATIENTS

From pyridine extracted alum complexed allergenic extracts to aqueous extracts and glycerinated: In order to avoid untoward reaction, it is recommended that therapy be initiated as though patients were previously untreated. The first dose should be related to the patient’s sensitivity, determined by history and confirmed by skin testing.

From unstandardized aqueous extracts to standardized aqueous extracts and glycerinated: The physician should establish the potency relationship, perhaps by comparative skin testing at equal concentration, prior to injecting the first standardized dose.

From aqueous alum precipitated or modified extracts to aqueous extracts and glycerinated: Since this subject has not been studied, it is recommended that therapy be initiated as if the patient were not previously treated.

PRECAUTIONS

INFORMATION TO PATIENTS:

Patients should be instructed to describe any active allergic symptoms such as rhinitis, wheezing, dyspnea, etc. prior to injection including any late reactions from previous administration. Patients should be instructed to remain in the office for 20 to 30 minutes after injection to monitor for adverse reactions. Also, see ADVERSE REACTIONS and WARNINGS Sections.

If the protective action of allergenic extract injections is considered essential for the patient’s welfare, appropriate symptomatic therapy with antihistaminic, adrenergic or other drugs might be needed either prior to or in conjunction with the allergenic extract injections.

GENERAL:

1. Objective assessment of pulmonary function such as Peak Expiratory Flow Rate (PEFR) before allergen administration may be useful in unstable asthmatic to reduce the chances of exacerbation of the patient’s asthma.
2. Store allergenic extracts between 2° and 8°C at all times, even during use.
3. Injections are to be given subcutaneously with the usual sterile precautions using a tuberculin syringe.
4. Care must be taken to avoid injecting into a blood vessel. Pull gently on syringe plunger to determine if a blood vessel has been entered (See WARNINGS).
5. Allergenic extracts slowly become less potent with age. During the course of treatment, it may be necessary to continue therapy with a vial of extract bearing a later expiration date. The initial dose of the extract bearing the later expiration date should be lowered to a safe, non-reaction eliciting level which can be confirmed by comparative skin testing using end-point titration.
6. Use standard aseptic precautions when making dilutions. The first dose of the new extract should be reduced to at least 25% of the amount of the dosage from the previous extract.
7. Extracts in 50% glycerin can cause discomfort at the site of the injection.

PREGNANCY - CATEGORY C:

Animal reproduction studies have not been conducted with allergenic extracts. It is also not known whether allergenic extracts can cause fetal harm when administered to a pregnant woman or can affect reproduction capacity.

Controlled studies of hyposensitization with moderate to high doses of allergenic extracts during conception and all trimesters of pregnancy have failed to demonstrate any risk to the fetus or to the mother. However, on the basis of histamine’s known ability to contract uterine muscle, the release of significant amounts of histamine from allergen exposure or hyposensitization overdose should be avoided on theoretical grounds. Therefore, allergenic extracts should be used cautiously in a pregnant woman and only if clearly needed.

PEDIATRIC USE:

Children can receive the same dose as adults, however, to minimize the discomfort associated with dose volume it may be advisable to reduce the volume of the dose by one-half and administer the injection at two different sites.

NURSING MOTHERS:

It is not known if allergens administered subcutaneously appear in human milk. Because many drugs are excreted in human milk, caution should be exercised when allergenic extracts are administered to a nursing woman.

CARCINOGENESIS, MUTAGENESIS, IMPAIRMENT OF FERTILITY:

Studies in animals have not been performed.

DRUG INTERACTIONS:

Drugs can interfere with the performance of skin tests.^6

Antihistamines: Response to mediator (histamine) released by allergens is suppressed by antihistamines. The length of suppression varies and is dependent on individual patient, type of antihistamine and length of time the patient has been on antihistamines. The duration of this suppression may be as little as 24 hours (chlorpheniramine), and can be as long as 40 days (astemizole).

Tricyclic Antidepressants: These exert a potent and sustained decrease of skin reactivity to histamine which may last for a few weeks.

Beta2 Agonists: Oral terbutaline and parenteral ephedrine, in general, have been shown to decrease allergen induced wheal.

Dopamine: Intravenous infusion of dopamine may inhibit skin test responses.

Beta Blocking Agents: Propranolol can significantly increase skin test reactivity (See WARNINGS).

Other Drugs: Short acting steroids, inhaled beta2 agonists, theophylline and cromolyn do not seem to affect skin test response.

ADVERSE REACTIONS

Anaphylaxis and deaths following the injection of mite and other extracts have been reported by The British Committee on Safety in Medicine.^7 Fatalities from immunotherapy in the United States since 1945 have been extensively reviewed by Lockey, R. F., et al^8 and more recently by Reid, M. J. et al.^9

With careful attention to dosage and administration, such reactions occur infrequently, but it must be remembered that allergenic extracts are highly potent to sensitive individuals and OVERDOSE could result in anaphylactic symptoms. Therefore, it is imperative that physicians administering allergenic extracts understand and be prepared for the treatment of severe reactions.

Local: Reactions at the site of injection may be immediate or delayed. Immediate wheal and erythema reactions are ordinarily of little consequence; but if very large, may be the first manifestation of a systemic reaction. If large local reactions occur, the patient should be observed for systemic symptoms for which treatment is outlined below.

Delayed reactions start several hours after injection with local edema, erythema, itching or pain. They are usually at their peak at 24 hours and usually require no treatment. Antihistamine drugs may be administered orally.

The next therapeutic dose should be reduced to the dose which did not elicit a reaction, and subsequent doses increased more slowly; i.e., use of intermediate dilutions.

Systemic: Systemic reactions are characterized by one or more of the following symptoms: Sneezing, mild to severe generalized urticaria, itching other than at the injection site, extensive or generalized edema, wheezing, asthma, dyspnea, cyanosis, tachycardia, lacrimation, marked perspiration, cough, hypotension, syncope and upper airway obstruction. Symptoms may progress to shock and death. Patients should always be observed for at least 20 to 30 minutes after any injection. Volume expanders and vasopressor agents may be required to reverse hypotension. Inhalational bronchodilators and parenteral aminophylline may be required to reverse bronchospasm. Severe airway obstruction, unresponsive to bronchodilator, may require tracheal intubation and use of oxygen. In the event of a marked systemic reaction, application of a tourniquet above the injection site and the administration of 0.2 mL to 1 mL of Epinephrine Injection (1:1,000) are recommended. Maximal recommended dose for children under 2 years of age is 0.3 mL. Maximal recommended dose for children between 2 and 12 years of age is 0.5 mL. The tourniquet should not be left in place without loosening for 90 seconds every 15 minutes.

The next therapeutic injection of extract should be reduced to the dose which did not elicit a reaction, and subsequent doses increased more slowly; i.e., use of intermediate dilutions.

OVERDOSAGE

Signs and symptoms of overdose are typically local and systemic reactions. For a description and management of overdose reactions, refer to “Adverse Reaction” section above.

DOSAGE AND ADMINISTRATION

Parenteral drug products should be inspected visually for particulate matter and discoloration prior to administration, whenever solution and container permit.

When diluting bulk extracts, use of Sterile Diluent for Allergenic Extracts or Sterile Diluent for Allergenic Extracts Normal Saline with HSA (albumin saline) is recommended. Dilutions should be made with sterile disposable syringes using aseptic technique. Commonly, 10 fold dilutions are used to achieve a desired concentration for initiation and continuation of immunotherapy. For example, transferring 0.5 mL of a 10,000 PNU/mL extract into 4.5 mL of diluent will yield 5 mL of extract at 1,000 PNU/mL. For weight volume products, a 1:100 w/v dilution may be prepared from a 1:10 w/v by transferring 0.5 mL of the 1:10 w/v to 4.5 mL of diluent. Prepare as many additional serial dilutions as necessary to reach the appropriate concentration.

Starting dose for immunotherapy is related directly to a patient’s sensitivity as determined by carefully executed skin testing. Degree of sensitivity can be established by determination of D50.^11 A general rule is to begin at 1/10 of the dose that produces sum of erythema of 50 mm (approximately a 2+ positive skin test reaction).

For example, if a patient exhibits a 2+ intradermal reaction to 1 AU/mL, the first dose should be no higher than 0.05 mL of 0.1 AU/mL. Dosage may be increased by 0.05 mL each time until 0.5 mL is reached, at which time the next 10-fold more concentrated dilution can be used, beginning with 0.05 mL, if no untoward reaction is observed.

Interval between doses in the early stages of immunotherapy is no more than once to twice a week, and may gradually be increased to once every two weeks. Generally, maintenance injections may be given as infrequently as once every two weeks to once a month.

Injections are given subcutaneously, preferably in the arm. It is advantageous to give injections in alternate arms and routinely in the same area. In some patients, a local tolerance to the allergen may develop thus preventing a possible severe local reaction.

Formal stability studies for diluted and undiluted forms of unstandardized extracts have not been performed; therefore, it is recommended that minimal amounts of the concentrate be diluted so that the diluted product is used up within a relatively short period of time; i.e., preferably not more than four weeks.

PRE-SEASONAL METHOD OF TREATMENT

Treatment of hay fever by the pre-seasonal method should be started 6-10 weeks prior to the usual onset of symptoms. Therapy should be started early enough to permit a graduated series of doses at 2-7 day intervals. It is recommended that the larger doses be spaced 5-7 days apart.

Some physicians continue therapy into or through the season by repeating a reduced or MAINTENANCE dose at weekly or biweekly intervals. If during the season, hay fever symptoms develop, relief may be provided by giving supplemental treatment. If the last dose was well-tolerated and not more than 2 weeks has elapsed since it was given, this dose may be given again and repeated every 4 to 7 days.

PERENNIAL TREATMENT

The patient’s tolerance to the offending pollen or pollens is first established by the injection of a series of graduated doses as outlined in the PRE-SEASONAL METHOD, not necessarily given pre-seasonally, since perennial therapy may be begun at any time. After completion of the ascending series of injections, from 1/4 to 1/2 of the highest well-tolerated dose is continued at 2 to 3 week intervals throughout the year. Shortly before the usual onset of symptoms (4 to 5 weeks prior to the season) the interval between injections is shortened and the dosage is gradually increased, according to the Pre-Seasonal schedule, until maximum well-tolerated dose is again attained. This top dose should be reached just before the usual onset of symptoms at which time the treatment is discontinued. If patient’s symptoms persist, therapy may be continued at a reduced dosage level, usually 1/4 to 1/2 of the top dose.

DOSAGE ADJUSTMENTS

For Products Containing Short Ragweed.

In transferring patients from unstandardized to standardized product, the physician should establish the potency relationships, perhaps by comparative skin testing, prior to injecting the first standardized dose.

AgE is important in adjusting dosage of Short Ragweed extracts to accurately transfer a patient from older extracts to fresher material. In such cases, the dosage of AgE should be considered in addition to the W/V dilution or protein nitrogen units. Antigen E concentration continuously declines in Short Ragweed Pollen extracts at a rate that varies with the formulation of the product. Aqueous extracts retain Antigen E potency less effectively than glycerin 50% (v/v) extracts. These differences are reflected in the expiration date declared on the vial. The continuous decline should be considered. Also, where ragweed is a component of an allergen mixture, clinical response to the other components must be considered in adjustment of dosage based on AgE content alone. The usual course of immunotherapy is three to five years.

Caution: A small percent of individuals allergic to Short Ragweed are more sensitive to minor antigens such as Ra3 Ra5 than AgE. There is no correlation between the amount of these antigens and either AgE or PNU content.

NOTE: For extracts of Short Ragweed or equal part mixture of Short and Tall Ragweed refer to AgE dosage schedule. The AgE content for those products is indicated on the vial label. The physician may use the formula below to determine the AgE dosage for each injection.

AgE dosage can be monitored by using the following formula:

W/V compounded products:

Labeled AgE X Dose (mL) = dose in AgE

PNU compounded products:

Labeled AgE/mL X dose in PNU = dose in AgE

Labeled PNU/mL

HOW SUPPLIED

1. Concentrate in multiple dose vials:
2. Sterile Diluent for Allergenic Extracts (Phenol Saline) is supplied in vials of 4.5 mL, 9.0 mL, 30 mL and 100 mL.

10 mL and 50 mL, single antigens or specified mixtures, potency expressed in PNU/mL (up to and including 100,000 PNU/mL) or W/V (up to and including 1:10 W/V), aqueous or in 50% glycerin, to be diluted prior to use. 1:10 w/v short ragweed extracts contain ≥ 300 units/mL of AgE.

STORAGE: To maintain stability of allergenic extracts, proper storage conditions are essential. Bulk concentrates and diluted extracts are to be stored at 2° to 8° C even during use. Bulk or diluted extracts are not to be frozen. Do not use after the expiration date shown on the vial label.

REFERENCES

1. Norman, P.S. et al: Immunotherapy of hayfever with ragweed antigen E. Comparisons with whole pollen extract and placebo. J. Allergy 42:93, 1968.
2. Van Metre, T.E. et al: A controlled study of the effectiveness of the Rinkel method of immunotherapy for ragweed pollen hayfever. J. Allergy Clin. Immunol. 65:288, 1980.
3. Umetsu, D.T. et al: Serum sickness triggered by anaphylaxis: a complication of immunotherapy. J. Allergy Clin. Immunol. 76:713, 1985.
4. Phannphak, P. and Kohler, P.F.: Onset of polyarteritis nodosa during allergic hyposenitization treatment. Am. J. Med. 68:479, 1980.
5. Kohler, P.F.: Immune complexes and allergic disease. In: Middleton et al: Allergy Principles and Practice 3rd Ed. St. Louis: CV Mosby, 1988:167.
6. Bousquet, J.: In vivo methods for the study of allergy: skin test, techniques, and interpretation. In: Middleton et al: Allergy Principles and Practice 3rd Ed. St. Louis: CV Mosby, 1988:167.
7. Committee on the Safety of Medicines. CSM update: desensitising vaccines. Brit Med. J. 293:948,1986.
8. Lockey, R.F. et al: Fatalities from immunotherapy (IT) and skin testing (ST). J. Allergy Clin. Immunol. 79:660, 1987.
9. Reid, M.J. et al: Survey of fatalities from skin testing and immunotherapy. 1985-1989. J. Allergy Clin. Immunol.;92:6, 1993.
10. Van Metre, T.E. et al: A controlled study of the effectiveness of the Rinkel method and the current standard method of immunotherapy for ragweed pollen hayfever. J. Allergy Clin. Immunol. 66:500, 1980.
11. Turkeltaub, P.C., Rastogi, S.C., Baer, H., et al: A standardized quantitative skin-test assay of allergen potency and stability: studies on the allergen dose-response curve and effect of wheal, erythema, and patient selection on assay results, J. Allergy Clin. Immunol. 70:343, 1982.

Revised April 2017 158M

© ALK-Abelló, Inc.

Distributed in Canada by:

ALK-Abelló Pharmaceuticals, Inc.

#35-151 Brunel Road

Mississauga, Ontario

Canada L4Z 2H6

PRINCIPAL DISPLAY PANEL

ALLERGENIC EXTRACT
mL sterile multiple dose vial